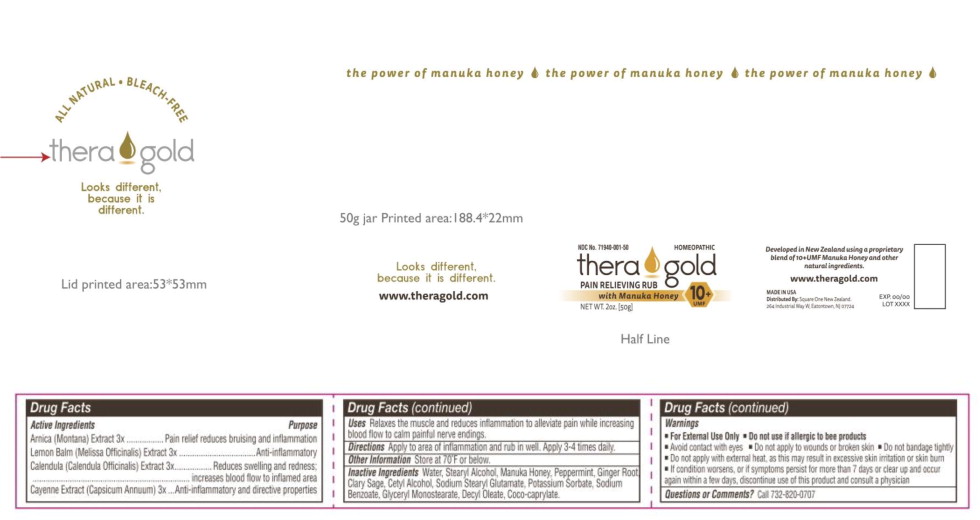 DRUG LABEL: Theragold
NDC: 71940-001 | Form: CREAM
Manufacturer: Square One New Zealand Llc.
Category: homeopathic | Type: HUMAN OTC DRUG LABEL
Date: 20180501

ACTIVE INGREDIENTS: Arnica Montana 3 [hp_X]/50 g; Melissa Officinalis Seed Oil 3 [hp_X]/50 g; Calendula Officinalis Flower 3 [hp_X]/50 g; Capsicum 3 [hp_X]/50 g
INACTIVE INGREDIENTS: Water; Stearyl Alcohol; Peppermint Oil; Ginger Oil; Honey; Clary Sage Oil; Cetyl Alcohol; Sodium Stearoyl Glutamate; Dimethicone; Potassium Sorbate; Sodium Benzoate; Glyceryl Monostearate

Drug Facts

Active Ingredients

Arnica (Montana) Extract 3x

Lemon Balm (Melissa Officinalis) Extract 3x

Calendula (Calendula Officinalis) Extract 3x

Caynne Extract (Capsicum Annuum) 3x

Purpose

Pain relief reduces bruising and inflammation

Anti-inflammatory

Reduces swelling and redness; increases blood flow to inflamed area

Anti-inflammatory and directive properties

Uses

Relaxes the muscle and reduces inflammation to alleviate pain while increasing blood flow to calm painful nerve endings.

Directions

Apply to area of inflammation and rub in well. Apply 3-4 times daily.

Other Information

Store at 70°F or below.

Inactive Ingredients

Water, Stearyl Alcohol, Manuka Honey, Peppermint, Ginger Root, Clary Sage, Cetyl Alcohol, Sodium Stearyl Glutamate, Potassium Sorbate, Sodium Benzoate, Glyceryl Monostearate, Decyl Oleate, Coco-caprylate.

Warnings

- For External Use Only

- Do not use if allergic to bee products
- Avoid contact with eyes
- Do not apply to wounds or broken skin
- Do not bandage tightly
- Do not apply with external heat, as this may result in excessive skin irritation or skin burn

KEEP OUT OF REACH OF CHILDREN

- If condition worsens, or if symptoms persist for more than 7 days or clear up and occur again within a few days, discontinue use of this product and consult a physician

Questions or Comments?

Call 732-820-0707

Principal Display Panel - TheraGold Jar Label

NDC No. 71940-001-50

HOMEOPATHIC

theragold

PAIN RELIEVING RUB

with Manuka Honey

10+
UMF

NET WT. 2oz. [50g]